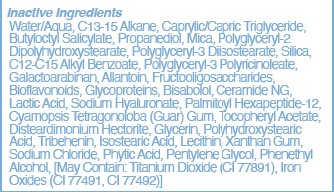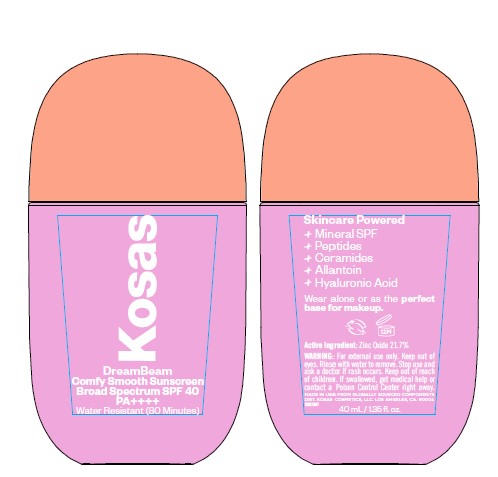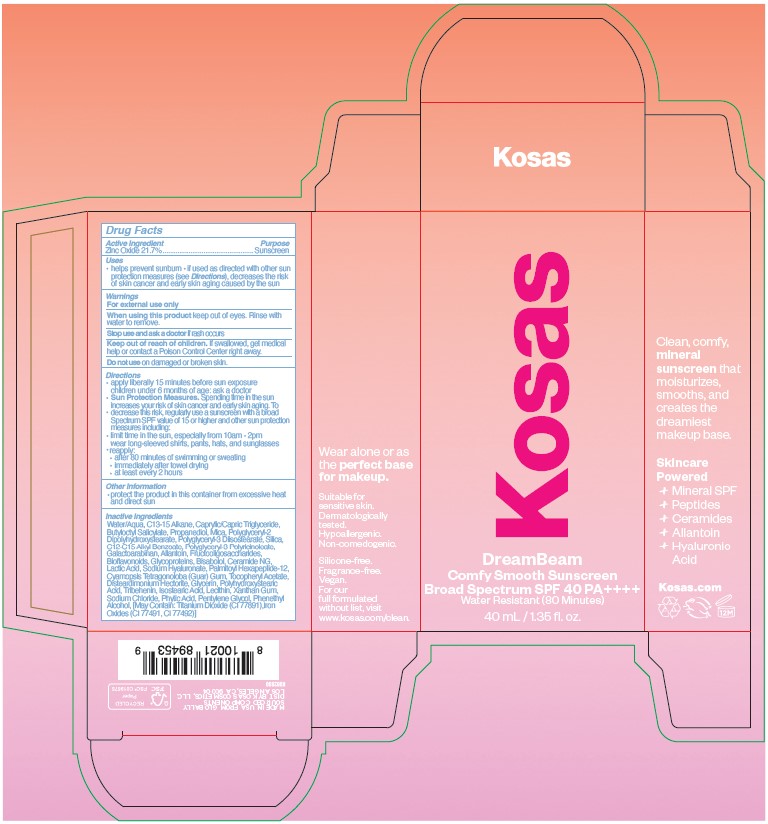 DRUG LABEL: DreamBeam Sunscreen
NDC: 82554-102 | Form: LOTION
Manufacturer: Kosas Cosmetics, LLC
Category: otc | Type: HUMAN OTC DRUG LABEL
Date: 20250213

ACTIVE INGREDIENTS: ZINC OXIDE 21.7 g/100 mL
INACTIVE INGREDIENTS: LEVOMENOL; BETA VULGARIS ROOT FRUCTOOLIGOSACCHARIDES; PHENYLETHYL ALCOHOL; CITRUS BIOFLAVONOIDS; PENTYLENE GLYCOL; TITANIUM DIOXIDE; FERRIC OXIDE RED; CERAMIDE NG; MEDIUM-CHAIN TRIGLYCERIDES; MICA; POLYGLYCERYL-2 DIPOLYHYDROXYSTEARATE; LACTIC ACID; SODIUM CHLORIDE; FYTIC ACID; XANTHAN GUM; CYAMOPSIS TETRAGONOLOBA WHOLE; TRIBEHENIN; ISOSTEARIC ACID; POLYHYDROXYSTEARIC ACID (2300 MW); .ALPHA.-TOCOPHEROL ACETATE; DISTEARDIMONIUM HECTORITE; GLYCERIN; PROPANEDIOL; HYALURONATE SODIUM; PALMITOYL HEXAPEPTIDE-12; LECITHIN, SOYBEAN; C13-15 ALKANE; BUTYLOCTYL SALICYLATE; ALKYL (C12-15) BENZOATE; GALACTOARABINAN; ALLANTOIN; WATER; SILICON DIOXIDE; POLYGLYCERYL-3 PENTARICINOLEATE; POLYGLYCERYL-3 DIISOSTEARATE; ALPHA-2-HS-GLYCOPROTEIN

Dosage

Directions:
Apply liberally 15 minutes before sun exposure.
Children under 6 months of age: ask a doctor.
Sun Protection Measures:

Spending time in the sun increases your risk of skin cancer and early skin aging.
Decrease this risk, regularly use a sunscreen with a broad Spectrum SPF value of 15 or higher and other sun protection measures including: limit time in the sun, especially from 10am - 2pm, wear long-sleeved shirts, pants, hats, and sunglasses.

Reapply after 80 minutes of swimming or sweating, immediately after towel drying, at least every 2 hours.

Warnings

For external use only.

When using this product keep out of eyes. Rinse with water to remove.

Stop use and ask a doctor is rash occurs.

Keep out of reach of children. If swallowed, get medical help or contact a Poison Control Center right away.

Do not use on damaged or broken skin.

Use

Helps prevent sunburn if used as directed with other sun protection measures (see Directions), decreases the risk of skin cancer and early skin aging caused by the sun.

Keep out of reach of children. If swallowed, get medical help or contact a Poison Control Center right away.

Purpose

Sunscreen